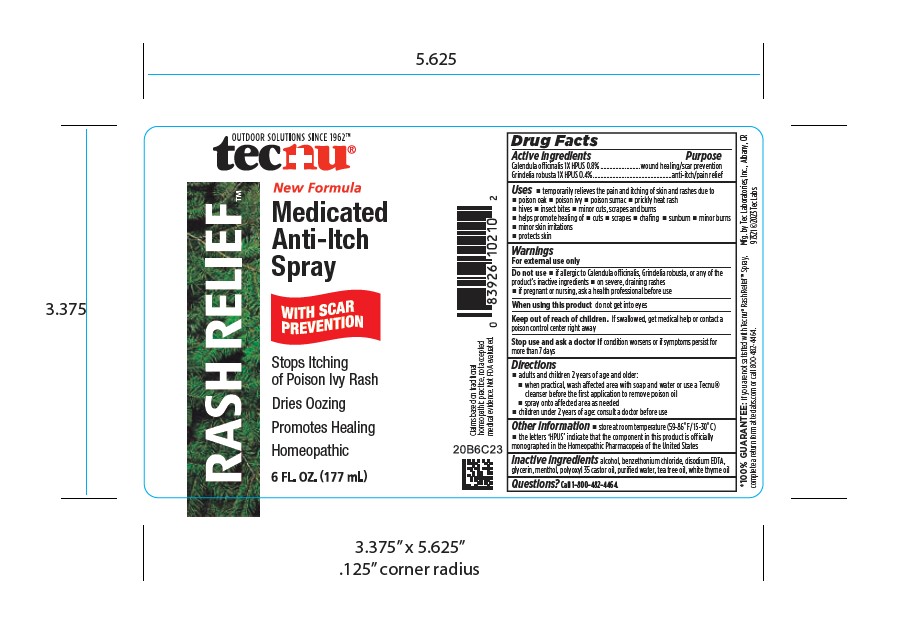 DRUG LABEL: Tecnu Rash Relief
NDC: 51879-164 | Form: SPRAY
Manufacturer: Tec Laboratories Inc.
Category: homeopathic | Type: HUMAN OTC DRUG LABEL
Date: 20241105

ACTIVE INGREDIENTS: GRINDELIA HIRSUTULA FLOWERING TOP 1 [hp_X]/1 mL; CALENDULA OFFICINALIS FLOWER 1 [hp_X]/1 mL
INACTIVE INGREDIENTS: ALCOHOL; THYME OIL; POLYOXYL 35 CASTOR OIL; EDETATE DISODIUM; BENZETHONIUM CHLORIDE; WATER; TEA TREE OIL; MENTHOL; GLYCERIN

Tecnu Rash Relief Spray

ACTIVE INGREDIENT

Grindelia Robusta 1X HPUS 0.8%

Calendual officinalis 1X HPUS 0.4%

PURPOSE

wound healing/ scar prevention

anti-itch/pain relief

Uses:

temporarily relieves the pain and itching of skin rashes due to

poison oak

poison ivy

poison sumac

prickly heat rash

hives

insect bites

minor cuts, scrapes and burns

helps promote healing of

cuts

scrapes

chafing

sunburn

minor burns

minor skin irritations

protects skin

WARNINGS

For external use only

Do not use:

if allergic to Calendula officinalis, Grindelia robusta, or any of the product's inactive ingredients

on severe, draining rashes

if pregnant or nursing, ask a health professional before use

When using this product:

do not get into eyes

Keep out of reach of children.

If swallowed, get medical help or contact a poison control center right away.

Stop use and ask a doctor if

condition worstens or if symptoms persist formore than 7 days

Directions

adults and children 2 years and older:

when practical, wash affected area with soap and water or use a Tecnu cleanser before the first appication to remove poison oil

spray onto affected area as needed

children 2 years of age: consult a doctor before use

Other information:

store at room temperature (59-86ºF/ 15-30ºC)

the letters "HPUS" indicate that the component in this product is officially monographed in the Homeopathic Pharmacopeia of the United States

Inactive ingredients

alcohol, bezethonium chloride, disodium EDTA, glycerin, menthol, polyoxyl 35 castor oil, purified water, tea tree oil, white thyme oil

Questions?

Call 1-800-482-4464

PACKAGE LABEL

OUTDOOR SOULUTIONS SINCE 1962

tecnu

Rash Relief

Medicated Anti-itch-Spray

With Scar Prevention

Stops Itching of Poison Ivy Rash

Dries Oozing

Promotes Healing

Homeopathic

6 FL. OZ. (177 mL)